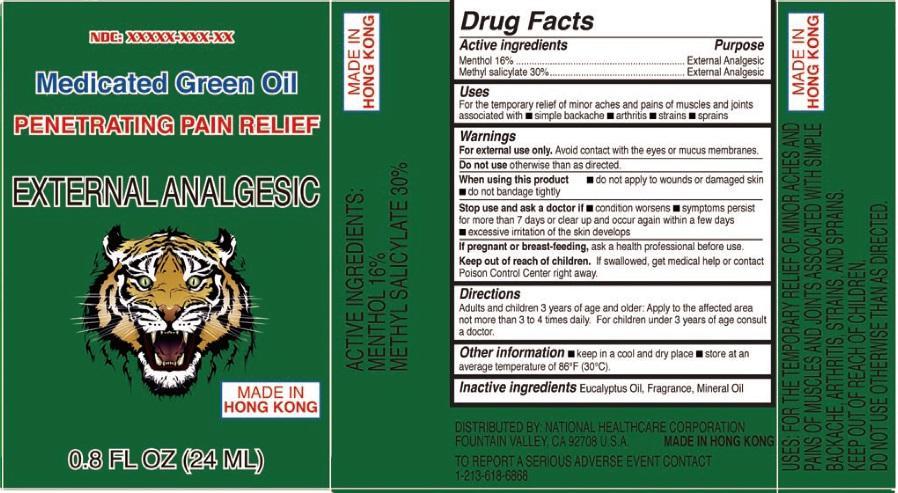 DRUG LABEL: Medicated Green Oil
NDC: 55531-001 | Form: OIL
Manufacturer: Allways Health-Care Corporation Limited
Category: otc | Type: HUMAN OTC DRUG LABEL
Date: 20130702

ACTIVE INGREDIENTS: MENTHOL 160 mg/100 mL; METHYL SALICYLATE 300 mg/100 mL
INACTIVE INGREDIENTS: EUCALYPTUS OIL; MINERAL OIL

Medicated Green Oil

Active Ingredient

Menthol 16%

Methyl salicylate 30%

Purpose

External Analgesic

Uses

For the temporary relief of minor aches and pains of muscles and joints associated with

simple backache

arthritis

strains

sprains

Warnings

For external use only. Avoid contact with the eyes or mucus membranes.

Do not use

other than as directed.

When using this product

do not apply to wounds or damaged skin

do not bandage tightly

Stop use and ask a doctor

if condition worsenes

symptoms persist for more than 7 days or clear up and occur again within a few days.

excessive irritation of the skin develops.

If pregnant or breast-feeding

ask a health professional before use.

Keep out of reach of children.

If swallowed, get medical help or contact Poison Control Center right away.

Directions

Adulst and children 3 years of age and older: Apply to the affected area not more than 3 to 4 times daily. For children under 3 years of age, consult a doctor.

Other information

keep in a cool and dry place.

Store at an average temperature of 86degrees F (30C)

Inactive Ingredients

Eucalyptus oil, fragrance, mineral oil

DISTRIBUTED BY: NATIONAL HEALTH CARE CORPORATION

FOUNTAIN VALLEY, CA 92708 U.S.A.

MADE IN HONG KONG

TO REPORT A SERIOUS ADVERSE EVENT CONTACT

1-213-618-6868